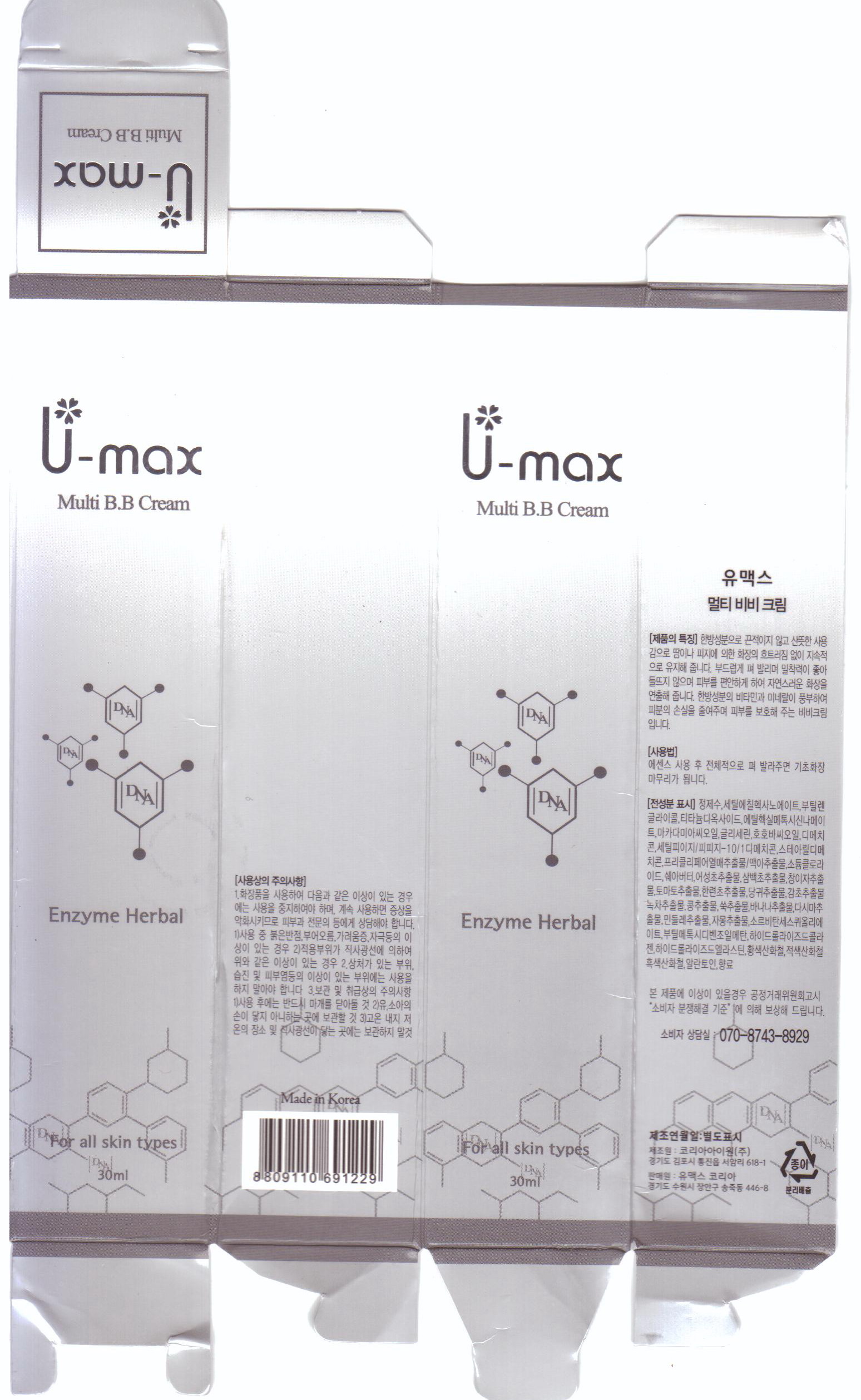 DRUG LABEL: U-max Multi BB
NDC: 50795-2001 | Form: CREAM
Manufacturer: VS Shinbi Co., Ltd.
Category: otc | Type: HUMAN OTC DRUG LABEL
Date: 20120604

ACTIVE INGREDIENTS: ALLANTOIN 0.1 mL/100 mL
INACTIVE INGREDIENTS: WATER; GLYCERIN; MACADAMIA NUT; HOUTTUYNIA CORDATA FLOWERING TOP; XANTHIUM STRUMARIUM FRUIT; SOLANUM LYCOPERSICUM; ANGELICA GIGAS ROOT; GLYCYRRHIZA GLABRA; ARTEMISIA VULGARIS ROOT; FERRIC OXIDE YELLOW; BANANA; FERRIC OXIDE RED; FERROSOFERRIC OXIDE; JOJOBA OIL; LAMINARIA JAPONICA; TARAXACUM OFFICINALE; CITRUS PARADISI SEED; CETYL ETHYLHEXANOATE; SORBITAN SESQUIOLEATE; OCTINOXATE; SHEA BUTTER; DIMETHICONE

Drug Facts

active ingredient: allantoin

inactive ingredient: macadamia ternifolia seed oil, simmondsia chinensis seed oil, cetyl ethylhexanoate, sorbitan sesquioleate, cetyl PEG/PPG10/1 dimethicone, ethylhexyl methoxycinnamate, hydrolyzed ellastin, butyl methoxydibenzoylmethane, shea butter, stearyl dimethicone, dimethicone, titanium dioxide, ci 77492, ci 77491, ci 44299, water, glycerin, butylene glycol, sodium chloride, hydrolyzed collagen, opuntia tuna fruit extract perform malt extract, houttuynia cordata extract, xanthium strumarium fruit extract, solanum lycopersicum fruit extract, clipta prostrata leaf extract, angelica gigas root extract, glycyrrhiza glabra root extract, camellia sinensis leaf extract, hydrolyzed soybean extract, artemisia vulgaris extract, laminaria japonica extract, taraxacum officinale leaf extract, citrus paradisi seed oil, musa sapientum fruit extract

PURPOSE

skin protectant (BB)

keep out of reach of the children

INDICATIONS AND USAGE

- apply only for skin
- apply 2 or 3 times a day with 5~6ml
- massage with your finger over 2 min and let them dry

WARNINGS

- keep out of eyes, ears and mouth
- if contact occurs, rinse away with plenty of cold water

DOSAGE AND ADMINISTRATION

- for external use only